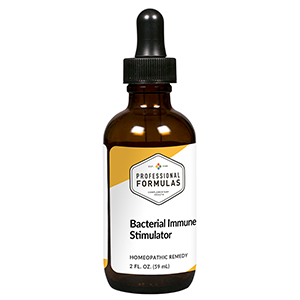 DRUG LABEL: Bacterial Immune Stimulator
NDC: 63083-6006 | Form: LIQUID
Manufacturer: Professional Complementary Health Formulas
Category: homeopathic | Type: HUMAN OTC DRUG LABEL
Date: 20190815

ACTIVE INGREDIENTS: ALOE 6 [hp_X]/59 mL; CALCIUM SULFIDE 6 [hp_X]/59 mL; GOLDENSEAL 6 [hp_X]/59 mL; SULFUR 6 [hp_X]/59 mL; GARLIC 12 [hp_X]/59 mL; GRAPHITE 12 [hp_X]/59 mL; ESCHERICHIA COLI 30 [hp_X]/59 mL; RANCID BEEF 30 [hp_X]/59 mL; BACILLUS ANTHRACIS IMMUNOSERUM RABBIT 30 [hp_X]/59 mL; DELPHINIUM STAPHISAGRIA SEED 30 [hp_X]/59 mL; DIPHTHERIAL RESPIRATORY PSEUDOMEMBRANE HUMAN 30 [hp_X]/59 mL; STREPTOCOCCUS PYOGENES 30 [hp_X]/59 mL; STAPHYLOCOCCUS AUREUS 30 [hp_X]/59 mL; TREPONEMIC SKIN CANKER HUMAN 30 [hp_X]/59 mL; CLOSTRIDIUM BOTULINUM 30 [hp_X]/59 mL; BOVINE TUBERCULIN 30 [hp_X]/59 mL; EUCALYPTOL 30 [hp_X]/59 mL; CANIS LUPUS FAMILIARIS MILK 30 [hp_X]/59 mL; COW MILK 30 [hp_X]/59 mL
INACTIVE INGREDIENTS: ALCOHOL; WATER

X6

ACTIVE INGREDIENTS

Aloe socotrina 6X
Hepar sulphuris calcareum 6X
Hydrastis canadensis 6X
Sulphur 6X
Allium sativum 12X
Graphites 12X, 30X
Bacillinum 30X, 60X
Pyrogenium 30X, 60X
Anthracinum 30X, 60X
Staphysagria 30X, 60X
Diphtherinum 30X, 60X
Streptococcinum 30X, 60X
Staphylococcinum 30X, 60X
Pneumococcinum 30X, 60X
Syphilinum 30X, 60X
Botulinum 30X, 60X
Tuberculinum 30X, 60X
Eucalyptol 30X
Lac caninum 30X
Lac vaccinum 30X

QUESTIONS

Professional Formulas

PO Box 2034 Lake Oswego, OR 97035

INDICATIONS

Temporarily reduces occasional mild abdominal pain or discomfort, nausea, headache, fatigue, runny nose, chills, or cough.*

PURPOSE

*Claims based on traditional homeopathic practice, not accepted medical evidence. Not FDA evaluated.

WARNINGS

Do not use for more than 30 days. Persistent symptoms may be a sign of a serious condition. If symptoms persist or are accompanied by a fever, rash, or persistent headache, consult a doctor. Keep out of the reach of children. In case of overdose, get medical help or contact a poison control center right away. If pregnant or breastfeeding, ask a healthcare professional before use.

Keep out of the reach of children.

PREGNANCY OR BREAST FEEDING

If pregnant or breastfeeding, ask a healthcare professional before use.

DIRECTIONS

Place drops under tongue 30 minutes before/after meals. Adults and children 12 years and over: Take 10 drops up to 3 times per day. Consult a physician for use in children under 12 years of age.

OTHER INFORMATION

Tamper resistant. If seal is broken, do not use. After opening, close container tightly and store at room temperature away from heat.

INACTIVE INGREDIENTS

20% ethanol, purified water.

LABEL

Est 1985

Professional Formulas

Complementary Health

Bacterial Immune Stimulator

Homeopathic Remedy

2 FL. OZ. (59 mL)